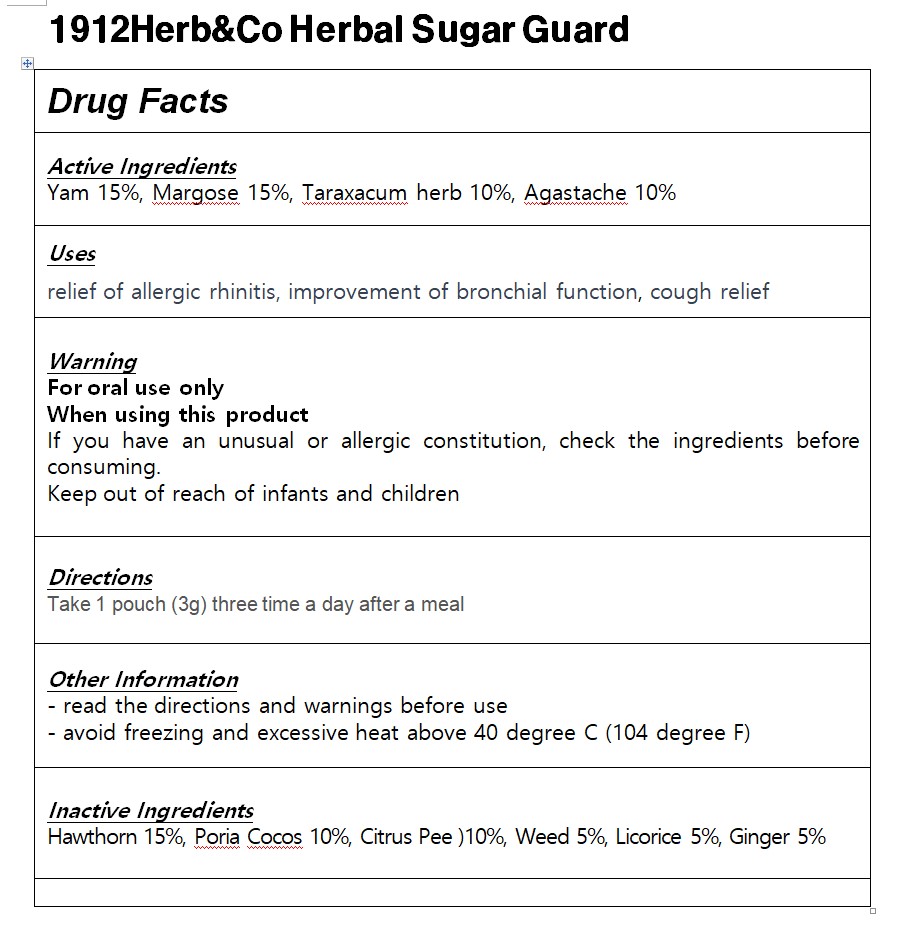 DRUG LABEL: 1912Herb Co Herbal Sugar Guard
NDC: 83933-0004 | Form: POWDER
Manufacturer: Agricultural Corporation YUBIMUHUAN CO Ltd
Category: otc | Type: HUMAN OTC DRUG LABEL
Date: 20241110

ACTIVE INGREDIENTS: TARAXACUM PALUSTRE ROOT 10 g/100 g
INACTIVE INGREDIENTS: PAEONIA LACTIFLORA ROOT

Drug Facts

ACTIVE INGREDIENT

Yam 15%, Margose 15%, Taraxacum herb 10%, Agastache 10%

INACTIVE INGREDIENT

Hawthorn 15%, Poria Cocos 10%, Citrus Pee)10%, Weed 5%, Licorice 5%, Ginger 5%

PURPOSE

digestive enhancement, relief of stomach pain, improvement of digestive function

keep out of reach of the children

INDICATIONS AND USAGE

Take 1 pouch (3g) three time a day after a meal

WARNINGS

If you have an unusual or allergic constitution, check the ingredients before consuming.

DOSAGE AND ADMINISTRATION

for oral use only